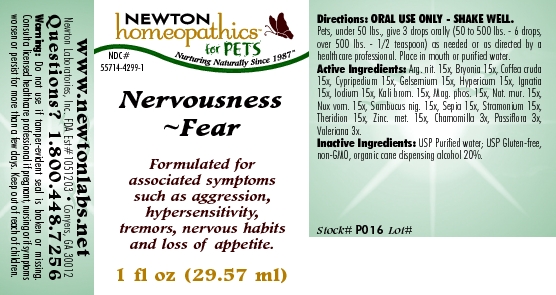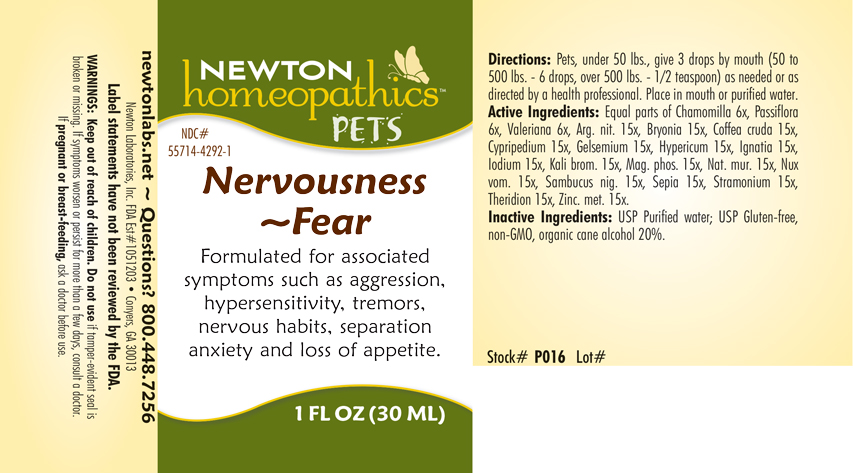 DRUG LABEL: Nervousness - Fear
NDC: 55714-4299 | Form: LIQUID
Manufacturer: Newton Laboratories, Inc.
Category: homeopathic | Type: OTC ANIMAL DRUG LABEL
Date: 20190114

ACTIVE INGREDIENTS: Silver Nitrate 15 [hp_X]/1 mL; Bryonia Alba Root 15 [hp_X]/1 mL; Arabica Coffee Bean 15 [hp_X]/1 mL; Cypripedium Parviflorum Var. Pubescens Root 15 [hp_X]/1 mL; Gelsemium Sempervirens Root 15 [hp_X]/1 mL; Hypericum Perforatum 15 [hp_X]/1 mL; Strychnos Ignatii Seed 15 [hp_X]/1 mL; Iodine 15 [hp_X]/1 mL; Potassium Bromide 15 [hp_X]/1 mL; Magnesium Phosphate, Dibasic Trihydrate 15 [hp_X]/1 mL; Sodium Chloride 15 [hp_X]/1 mL; Strychnos Nux-vomica Seed 15 [hp_X]/1 mL; Sambucus Nigra Flowering Top 15 [hp_X]/1 mL; Sepia Officinalis Juice 15 [hp_X]/1 mL; Datura Stramonium 15 [hp_X]/1 mL; Theridion Curassavicum 15 [hp_X]/1 mL; Zinc 15 [hp_X]/1 mL; Matricaria Recutita 3 [hp_X]/1 mL; Passiflora Incarnata Flowering Top 3 [hp_X]/1 mL; Valerian 3 [hp_X]/1 mL
INACTIVE INGREDIENTS: Alcohol

Nervousness - Fear

INDICATIONS & USAGE SECTION

Formulated for associated symptoms such as aggression, hypersensitivity, tremors, nervous habits, separation anxiety and loss of appetite.

DOSAGE & ADMINISTRATION SECTION

Directions: Pets, under 50 lbs., give 3 drops by mouth (50 to 500 lbs. - 6 drops, over 500 lbs. - 1/2 teaspoon) as needed or as directed by a health professional. Place in mouth or purified water.

OTC - ACTIVE INGREDIENT SECTION

Equal parts of Chamomilla 6x, Passiflora 6x, Valeriana 6x, Arg. nit. 15x, Bryonia 15x, Coffea cruda 15x, Cypripedium 15x, Gelsemium 15x, Hypericum 15x, Ignatia 15x, Iodium 15x, Kali brom. 15x, Mag. phos. 15x, Nat. mur. 15x, Nux vom. 15x, Sambucus nig. 15x, Sepia 15x, Stramonium 15x,Theridion 15x, Zinc. met. 15x.

OTC - PURPOSE SECTION

Formulated for associated symptoms such as aggression, hypersensitivity, tremors, nervous habits, separation anxiety and loss of appetite.

INACTIVE INGREDIENT SECTION

Inactive Ingredients: USP Purified Water; USP Gluten-free, non-GMO, organic cane alcohol 20%

QUESTIONS SECTION

newtonlabs.net - Questions? 800.448.7256
Newton Laboratories, Inc. FDA Est # 1051203 - Conyers, GA 30013

WARNINGS SECTION

WARNINGS: Do not use if tamper-evident seal is broken or missing. If symptoms worsen or persist for more than a few days, consult a doctor. If pregnant or breast-feeding, ask a doctor before use.

OTC - PREGNANCY OR BREAST FEEDING SECTION

If pregnant or breast-feeding, ask a doctor before use.

OTC - KEEP OUT OF REACH OF CHILDREN SECTION

Keep out of reach of children.